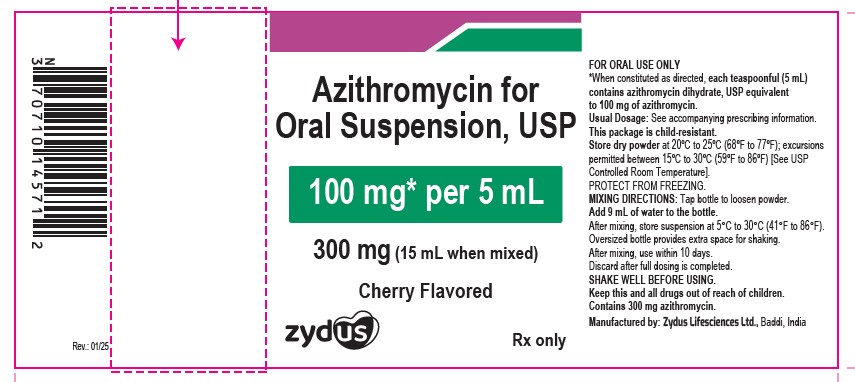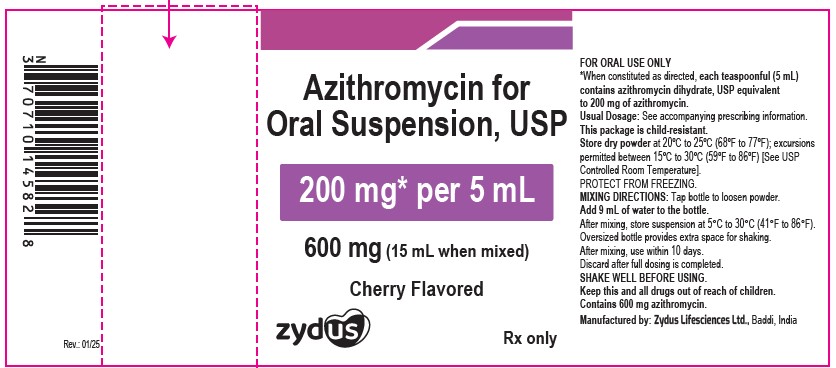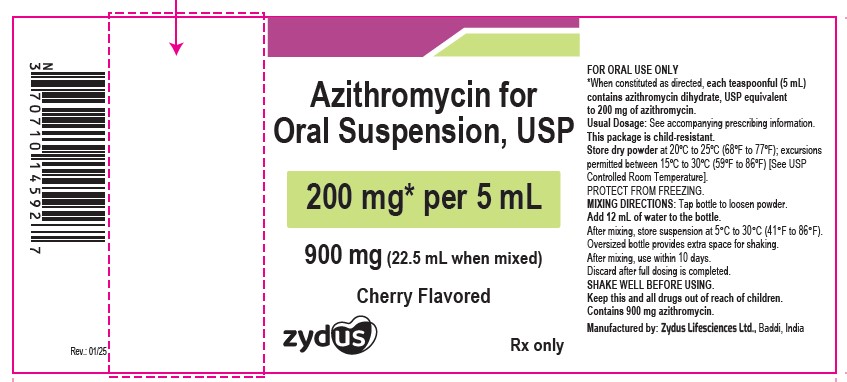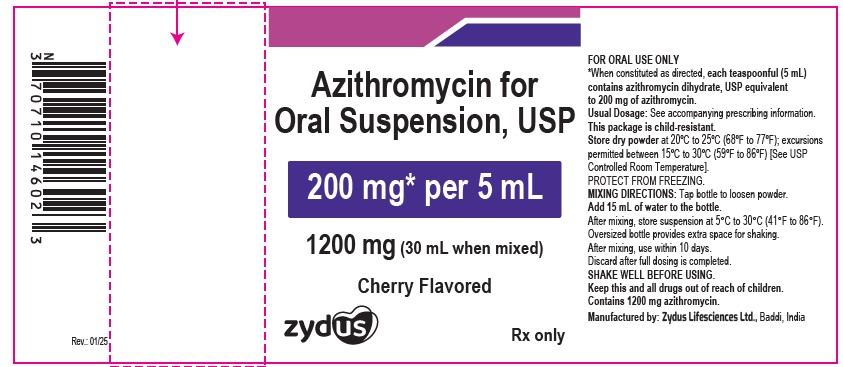 DRUG LABEL: Azithromycin
NDC: 70771-1422 | Form: POWDER, FOR SUSPENSION
Manufacturer: Zydus Lifesciences Limited
Category: prescription | Type: HUMAN PRESCRIPTION DRUG LABEL
Date: 20250109

ACTIVE INGREDIENTS: AZITHROMYCIN DIHYDRATE 100 mg/5 mL
INACTIVE INGREDIENTS: FD&C RED NO. 40; HYDROXYPROPYL CELLULOSE (90000 WAMW); SODIUM PHOSPHATE, TRIBASIC, ANHYDROUS; SUCROSE; XANTHAN GUM

AZITHROMYCIN FOR ORAL SUSPENSION

PACKAGE LABEL.PRINCIPAL DISPLAY PANEL

NDC 70771-1422-1

Azithromycin for oral suspension, 300 mg

100 mg/5 mL

Rx only

NDC 70771-1423-2

Azithromycin for oral suspension, 600 mg

200 mg/5 mL

Rx only

NDC 70771-1424-2

Azithromycin for oral suspension, 900 mg

200 mg/5 mL

Rx only

NDC 70771-1425-2

Azithromycin for oral suspension, 1200 mg

200 mg/5 mL

Rx only